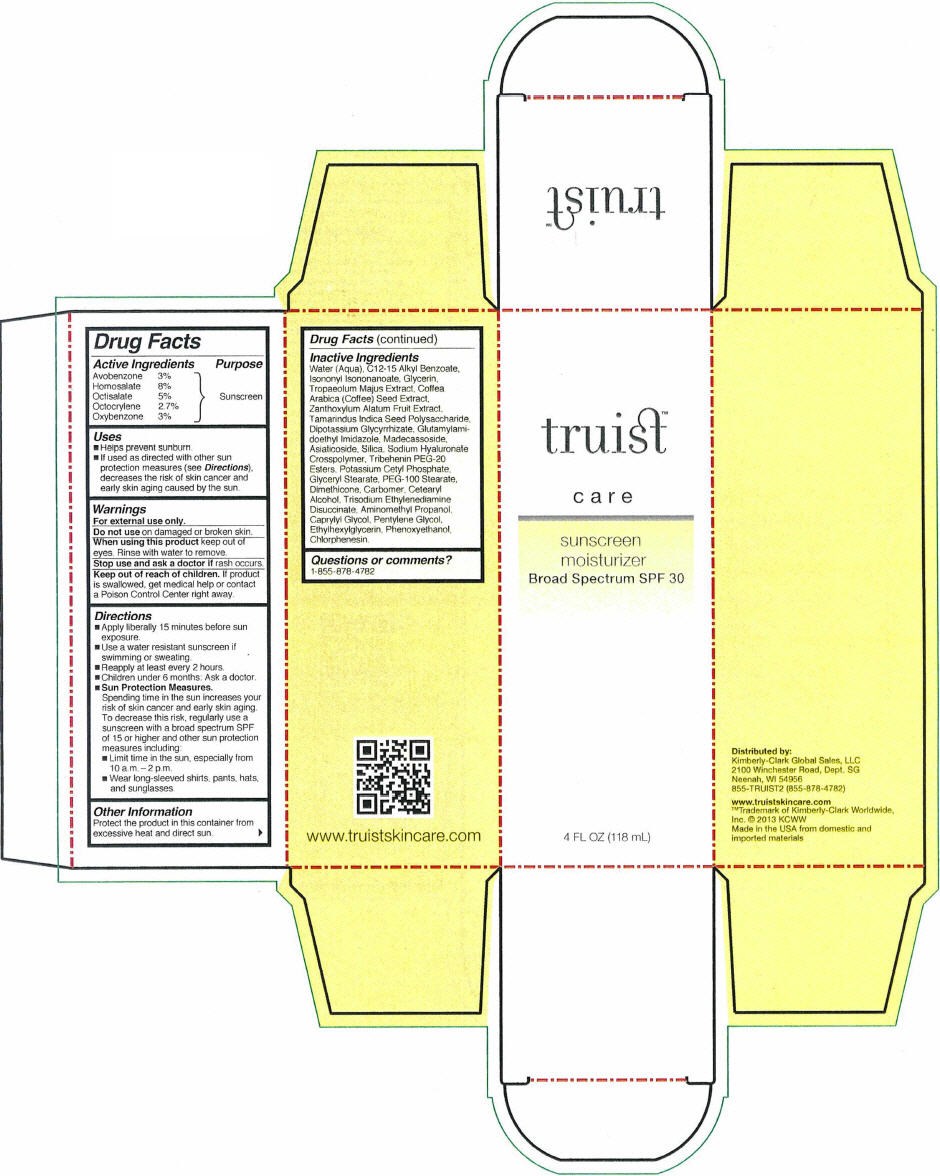 DRUG LABEL: Truist Sunscreen Moisturizer
NDC: 55118-605 | Form: LOTION
Manufacturer: Kimberly-Clark
Category: otc | Type: HUMAN OTC DRUG LABEL
Date: 20191017

ACTIVE INGREDIENTS: Avobenzone 30 mg/1 mL; HOMOSALATE 80 mg/1 mL; Octisalate 50 mg/1 mL; Octocrylene 27 mg/1 mL; Oxybenzone 30 mg/1 mL
INACTIVE INGREDIENTS: Water; Alkyl (C12-15) Benzoate; Isononyl Isononanoate; Glycerin; Tropaeolum Majus; Arabica Coffee Bean; ZANTHOXYLUM ARMATUM FRUIT; Glycyrrhizinate Dipotassium; Asiaticoside; Silicon Dioxide; Hyaluronate Sodium; Tribehenin PEG-20 Esters; Potassium Cetyl Phosphate; Glyceryl Monostearate; PEG-100 Stearate; Dimethicone; Cetostearyl Alcohol; Trisodium Ethylenediamine Disuccinate; Phenoxyethanol; Aminomethylpropanol; Caprylyl Glycol; Pentylene Glycol; Ethylhexylglycerin; Chlorphenesin

Truist™ Sunscreen Moisturizer

Drug Facts

Active Ingredients

Avobenzone 3%

Homosalate 8%

Octisalate 5%

Octocrylene 2.7%

Oxybenzone 3%

Purpose

Sunscreen

Uses

- Helps prevent sunburn.
- If used as directed with other sun protection measures (see Directions), decreases the risk of skin cancer and early skin aging caused by the sun.

Warnings

For external use only.

Do not use on damaged or broken skin.

When using this product keep out of eyes. Rinse with water to remove.

Stop use and ask a doctor if rash occurs.

Keep out of reach of children. If product is swallowed, get medical help or contact a Poison Control Center right away.

Directions

- Apply liberally 15 minutes before sun exposure.
- Use a water resistant sunscreen if swimming or sweating.
- Reapply at least every 2 hours.
- Children under 6 months: Ask a doctor.
- Sun Protection Measures.
  Spending time in the sun increases your risk of skin cancer and early skin aging. To decrease this risk, regularly use a sunscreen with a broad spectrum SPF of 15 or higher and other sun protection measures including:
  - Limit time in the sun, especially from 10 a.m. – 2 p.m.
  - Wear long-sleeved shirts, pants, hats, and sunglasses.

Other Information

Protect the product in this container from excessive heat and direct sun.

Inactive Ingredients

Water (Aqua), C12-15 Alkyl Benzoate, Isononyl Isononanoate, Glycerin, Tropaeolum Majus Extract, Coffea Arabica (Coffee) Seed Extract, Zanthoxylum Alatum Fruit Extract, Tamarindus Indica Seed Polysaccharide, Dipotassium Glycyrrhizate, Glutamylamidoethyl Imidazole, Madecassoside, Asiaticoside, Silica, Sodium Hyaluronate Crosspolymer, Tribehenin PEG-20 Esters, Potassium Cetyl Phosphate, Glyceryl Stearate, PEG-100 Stearate, Dimethicone, Carbomer, Cetearyl Alcohol, Trisodium Ethylenediamine Disuccinate, Aminomethyl Propanol, Caprylyl Glycol, Pentylene Glycol, Ethylhexylglycerin, Phenoxyethanol, Chlorphenesin.

Questions or comments?

1-855-878-4782

Distributed by:
Kimberly-Clark Global Sales, LLC
2100 Winchester Road, Dept. SG
Neenah, WI 54956

PRINCIPAL DISPLAY PANEL - 118 mL Bottle Label

truist™

care

sunscreen
moisturizer
Broad Spectrum SPF 30

4 FL OZ (118 mL)